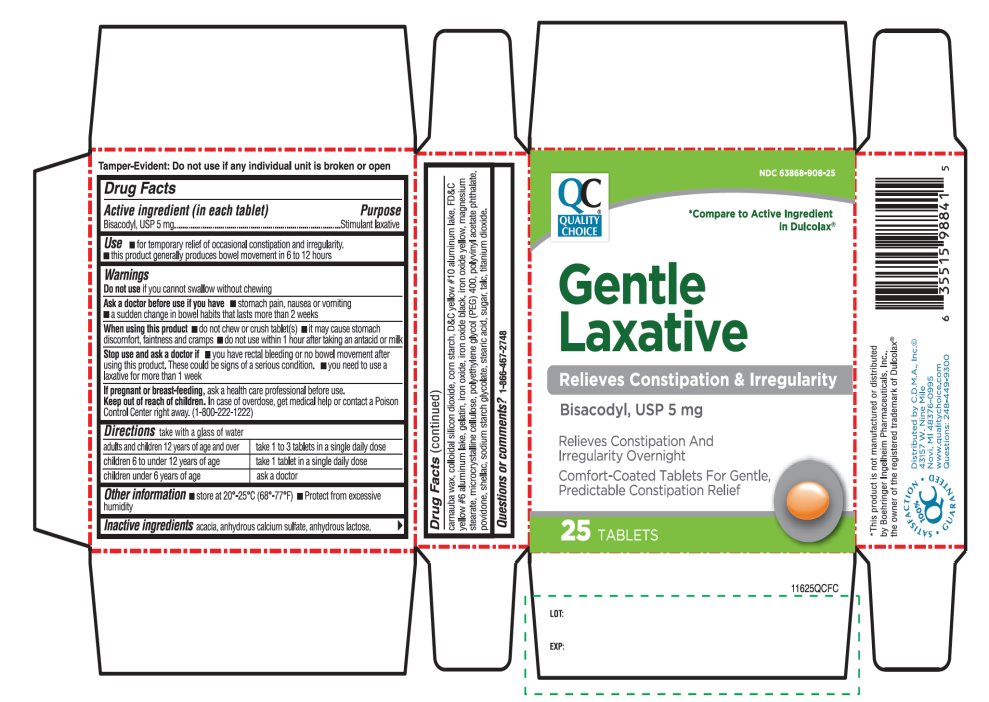 DRUG LABEL: Gentle Laxative

NDC: 63868-908 | Form: TABLET, COATED
Manufacturer: QUALITY CHOICE (CHAIN DRUG MARKETING ASSOCIATION)
Category: otc | Type: HUMAN OTC DRUG LABEL
Date: 20251203

ACTIVE INGREDIENTS: BISACODYL 5 mg/1 1
INACTIVE INGREDIENTS: ACACIA; CALCIUM SULFATE ANHYDROUS; ANHYDROUS LACTOSE; CARNAUBA WAX; SILICON DIOXIDE; STARCH, CORN; D&C YELLOW NO. 10; FD&C YELLOW NO. 6; GELATIN, UNSPECIFIED; FERROSOFERRIC OXIDE; FERRIC OXIDE RED; FERRIC OXIDE YELLOW; MAGNESIUM STEARATE; MICROCRYSTALLINE CELLULOSE; POLYETHYLENE GLYCOL 400; POLYVINYL ACETATE PHTHALATE; POVIDONE, UNSPECIFIED; SHELLAC; SODIUM STARCH GLYCOLATE TYPE A POTATO; STEARIC ACID; SUCROSE; TALC; TITANIUM DIOXIDE

Quality Choice Gentle Laxative 25 Tablets

Active ingredient (in each tablet)

Bisacodyl, USP 5 mg

Purpose

Stimulant laxative

Use

- for temporary relief of occasional constipation and irregularity
- this product generally produces a bowel movement in 6 to 12 hours

Warnings

Do not use

if you cannot swallow without chewing.

Ask a doctor before use if you have

- stomach pain, nausea or vomiting
- a sudden change in bowel habits that lasts more than 2 weeks

When using this product

- do not chew or crush tablet(s)
- do not use within 1 hour after taking an antacid or milk
- it may cause stomach discomfort, faintness and cramps

Stop use and ask a doctor if

- you have rectal bleeding or no bowel movement after using this product. These could be signs of a serious condition.
- you need to use a laxative for more than 1 week

If pregnancy or breast-feeding,

ask a health professional before use.

Keep out of reach of children.

In case of overdose, get medical help or contact a Poison Control Center right away. (1-800-222-1222).

Directions

take with a glass of water

adults and children 12 years of age and over | take 1 to 3 tablets in a single daily dose
children 6 to under 12 years of age | take 1 tablet in a single daily dose
children under 6 years of age | ask a doctor

Other information

- store at 20-25ºC (68º-77ºF)
- Protect from excessive humidity

Inactive ingredients

acacia, anhydrous calcium sulfate, anhydrous lactose, carnauba wax, colloidal silicon dioxide, corn starch, D&C yellow #10 aluminum lake, FD&C yellow #6 aluminum lake, gelatin, iron oxide, iron oxide black, iron oxide yellow, magnesium stearate, microcrystalline cellulose, polyethylene glycol (PEG) 400, polyvinyl acetate phthalate, povidone, shellac, sodium starch glycolate, stearic acid, sugar, talc, titanium dioxide.

Questions or comments?

1-866-467-2748

Principal Display Panel

NDC# 63868-908-25

*Compare to the Active Ingredient in Dulcolax®

Gentle Laxative

Relieves Constipation & Irregularity

Bisacodyl, USP 5 mg

Relieves Constipation And Irregularity Overnight

Comfort-Coated Tablets For Gentle, Predictable Constipation Relief

25 TABLETS

100% QC SATISFACTION GURANTEED

*This product is not manufactured or distributed by Boehringer Ingelheim Pharmaceuticals, Inc., the owner of the registered trademark Dulcolax®.

TAMPER EVIDENT: DO NOT USE IF any individual unit is broken or open.

Distributed by C.D.M.A., Inc.

43157 W. Nine Mile

Novi, MI 48376-0995

www.qualitychoice.com

Questions: 248-449-9300